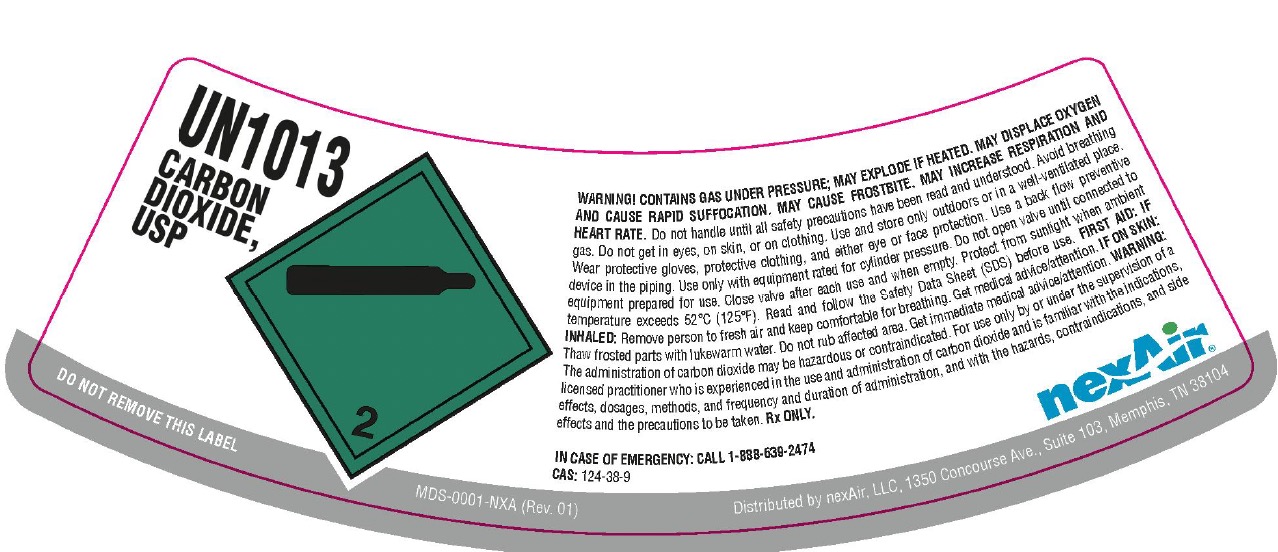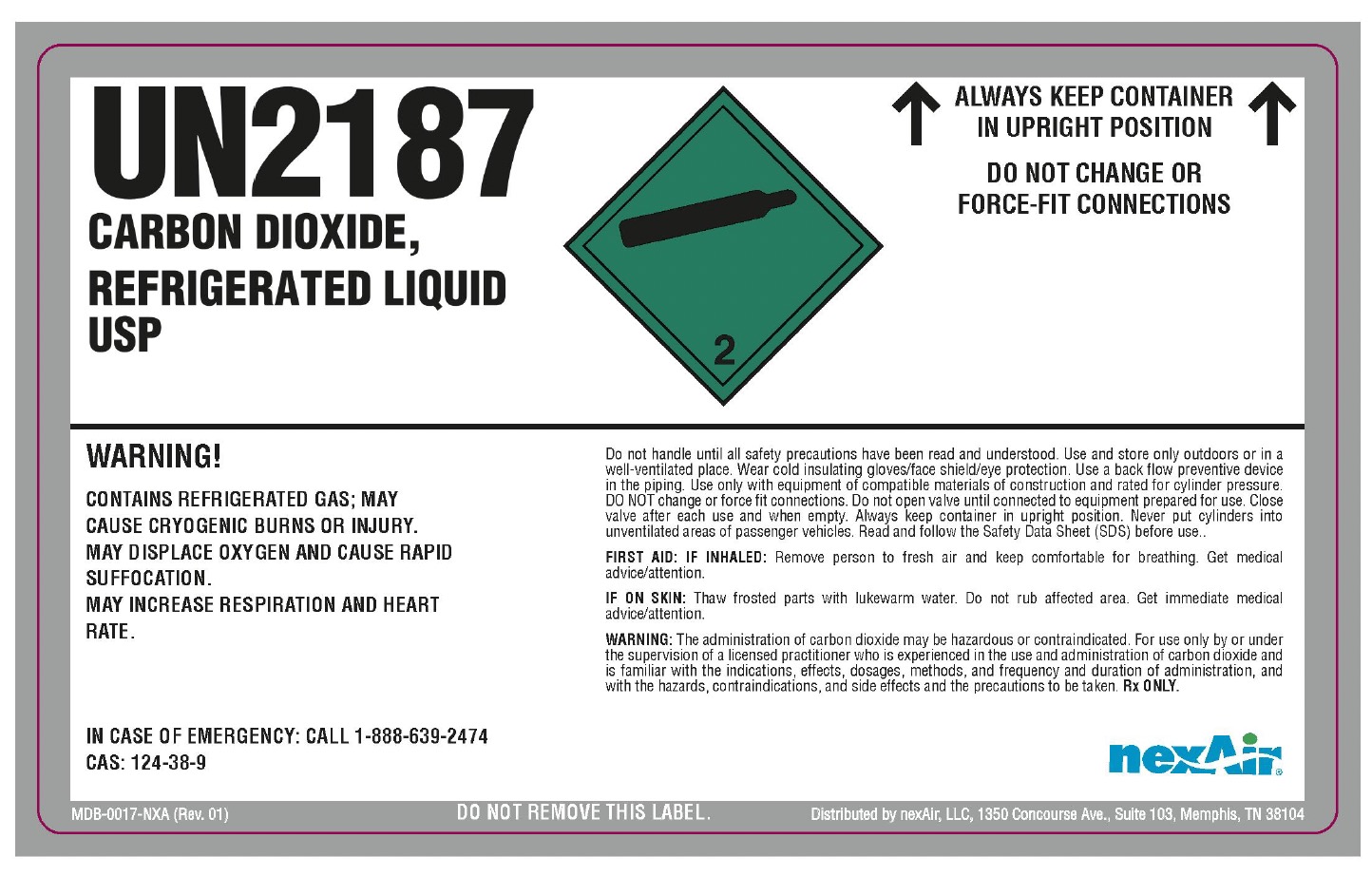 DRUG LABEL: Carbon Dioxide
NDC: 12213-901 | Form: GAS
Manufacturer: NexAir, LLC
Category: animal | Type: PRESCRIPTION ANIMAL DRUG LABEL
Date: 20251111

ACTIVE INGREDIENTS: CARBON DIOXIDE 991 mL/1 L

Carbon Dioxide

PACKAGE LABEL

UN1013
CARBON DIOXIDE, USP
DO NOT REMOVE THIS LABEL
WARNING! CONTAINS GAS UNDER PRESSURE; MAY EXPLODE IF HEATED. MAY DISPLACE OXYGEN AND CAUSE RAPID SUFFOCATION. MAY CAUSE FROSTBITE. MAY INCREASE RESIPRATION AND HEART RATE. Do not handle until all safety precautions have been read and understood. Avoid breathing gas. Do not get in eyes, on skin, or on clothing. Use and store only outdoors or in a well-ventilated place. Wear protective gloves, protective clothing, and either eye or face protection. Use a back flow preventive device in the piping. Use only with equipment rated for cylinder pressure. Do not open valve until connected to equipment prepared for use. Close valve after each use and when empty. Protect from sunlight when ambient temperature exceeds 52 C (125 F). Read and follow the Safety Data Sheet (SDS) before use. FIRST AID: IF INHALED: Remove person to fresh air and keep comfortable for breathing. Get medical advice/attention. IF ON SKIN: Thaw frosted parts with lukewarm water. Do not rub affected area. Get immediate medical advice/attention. WARNING: The administration of carbon dioxide may be hazardous or contraindicated. For use only by or under the supervision of a licensed practitioner who is experienced in the use and administration of carbon dioxide and is familiar with the indications, effects, dosages, methods, and frequency and duration of administration, and with the hazards, contraindications, and side effects and the precautions to be taken. Rx ONLY.
IN CASE OF EMERGENCY: CALL 1-888-639-2474
CAS: 124-38-9
nexAir
Distributed by nexAir, LLC, 1350 Concourse Ave., Suite 103, Memphis, TN 38104

PACKAGE LABEL

UN2187
CARBON DIOXIDE, REFRIGERATED LIQUID USP
WARNING!
CONTAINS REFRIGERATED GAS; MAY CAUSE CRYOGENIC BURNS OR INJURY. MAY DISPLACE OXYGEN AND CAUSE RAPID SUFFOCATION. MAY INCREASE RESPIRATION AND HEART RATE.
IN CASE OF EMERGENCY: CALL 1-888-639-2474
CAS: 124-38-9
ALWAYS KEEP CONTAINER IN UPRIGHT POSITION
DO NOT CHANGE OR FORCE-FIT CONNECTIONS
Do not handle until all safety precautions have been read and understood. Use and store only outdoors or in a well-ventilated place. Wear cold insulating gloves/face shield/eye protection. Use a back flow preventive device in the piping. Use only with equipment of compatible materials of construction and rated for cylinder pressure. DO NOT change or force fit connections. Do not open valve until connected to equipment prepared for use. Close valve after each use and when empty. Always keep container in upright position. Never put cylinders into unventilated areas of passenger vehicles. Read and follow the Safety Data Sheet (SDS) before use.
FIRST AID: IF INHALED: Remove person to fresh air and keep comfortable for breathing. Get medical advice/attention.
IF ON SKIN: Thaw frosted parts with lukewarm water. Do not rub affected area. Get immediate medical advice/attention.
WARNING: The administration of carbon dioxide may be hazardous or contraindicated. For use only by or under the supervision of a licensed practitioner who is experienced in the use and administration of carbon dioxide and is familiar with the indications, effects, dosages, methods, and frequency and duration of administration, and with the hazards, contraindications, and side effects and the precautions to be taken. Rx ONLY.
DO NOT REMOVE THIS LABEL.
nexAir
Distributed by nexAir, LLC, 1350 Concourse Ave., Suite 103, Memphis, TN 38104